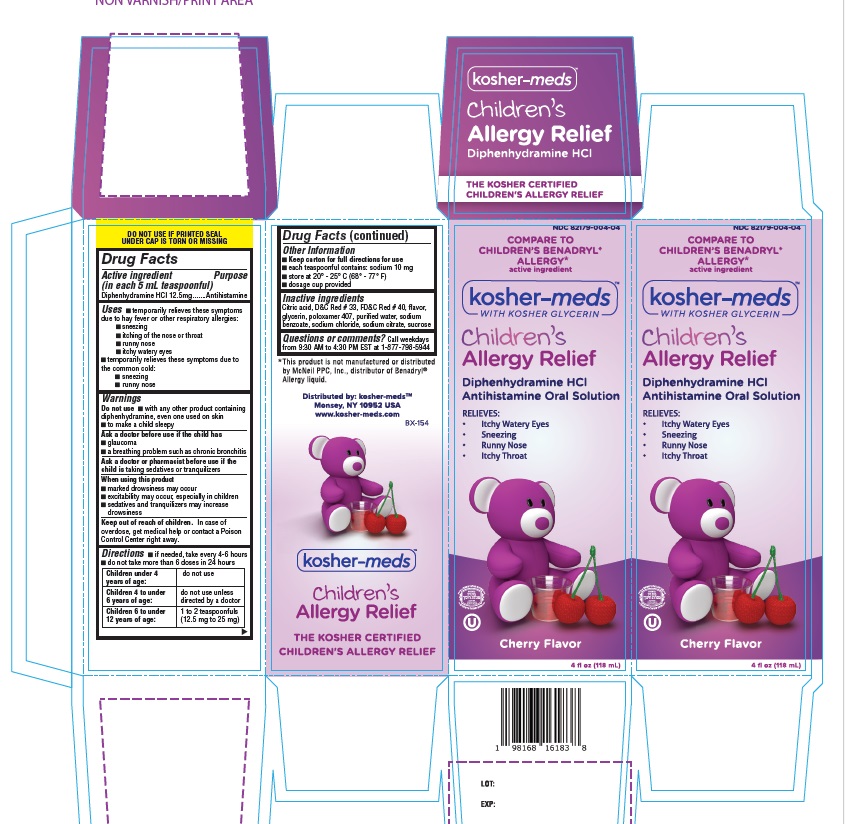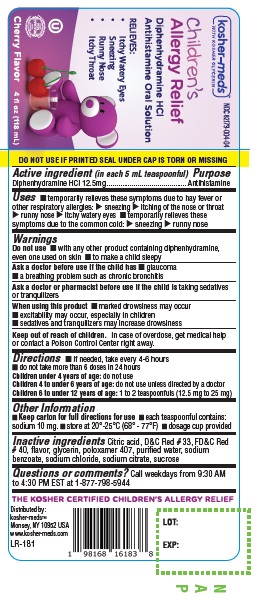 DRUG LABEL: Kosher Meds Childrens Allergy Relief
NDC: 82179-004 | Form: SOLUTION
Manufacturer: Mollec Inc
Category: otc | Type: HUMAN OTC DRUG LABEL
Date: 20240515

ACTIVE INGREDIENTS: DIPHENHYDRAMINE HYDROCHLORIDE 12.5 mg/5 mL
INACTIVE INGREDIENTS: CITRIC ACID MONOHYDRATE; FD&C RED NO. 40; GLYCERIN; POLOXAMER 407; WATER; SODIUM BENZOATE; SODIUM CHLORIDE; SODIUM CITRATE, UNSPECIFIED FORM; SUCROSE; D&C RED NO. 33

Active Ingredient

(in each 5 mL teaspoonful)
Diphenhydramine HCl 12.5mg

Purpose

Antihistamine

Uses

- temporarily relieves these symptoms due to hay fever or other respiratory allergies:
- sneezing
- itching of the nose or throat
- runny nose
- itchy watery eyes
- temporarily relieves these symptoms due to the common cold:
- sneezing
- runny nose

Warnings

Do not use

- with any other product containing diphenhydramine, even one used on skin
- to make a child sleepy

Ask a doctor before use if the child has

- glaucoma
- a breathing problem such as chronic bronchitis

Ask a doctor or pharmacist before use if the child istaking sedatives or tranquilizers

When using this product

- marked drowsiness may occur
- excitability may occur, especially in children
- sedatives and tranquilizers may increase drowsiness

Keep out of reach of children.In case of overdose, get medical help or contact a Poison Control Center right away.

Directions

- if needed, take every 4-6 hours
- do not take more than 6 doses in 24 hours

Children under 4 years of age: | do not use
Children 4 to under 6 years of age: | do not use unless directed by a doctor
Children 6 to under 12 years of age: | 1 to 2 teaspoonfuls (12.5 mg to 25 mg)

Other Information

- Keep carton for full directions for use
- each teaspoonful contains: sodium 10 mg
- store at 20° - 25° C (68° - 77° F)
- dosage cup provided

Inactive ingredients

Citric acid, D&C Red # 33, FD&C Red # 40, flavor, glycerin, poloxamer 407, purified water, sodium benzoate, sodium chloride, sodium citrate, sucrose

Questions or comments?

Call weekdays from 9:30 AM to 4:30 PM EST at 1-877-798-5944